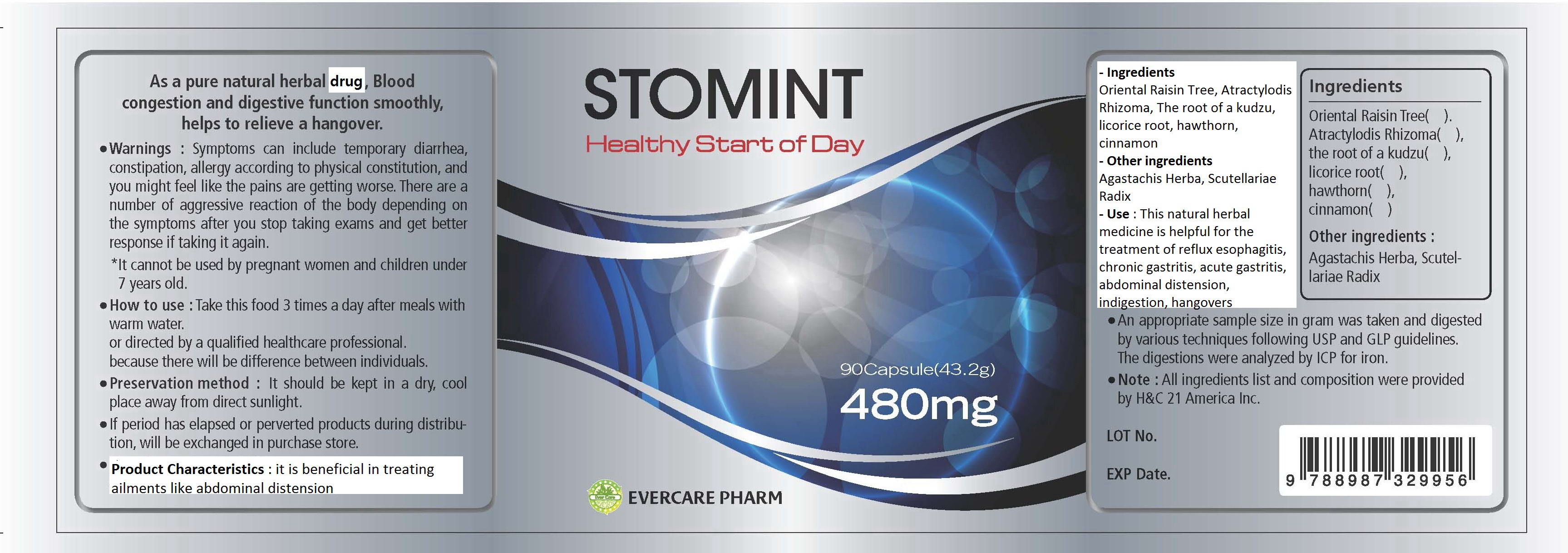 DRUG LABEL: Stomint
NDC: 42469-2001 | Form: TABLET
Manufacturer: Evercarepharm Co., Ltd
Category: otc | Type: HUMAN OTC DRUG LABEL
Date: 20120606

ACTIVE INGREDIENTS: ATRACTYLODES LANCEA ROOT 70 mg/1 1
INACTIVE INGREDIENTS: HOVENIA DULCIS FRUIT; CRATAEGUS MONOGYNA FRUIT; PUERARIA MONTANA VAR. LOBATA ROOT; GLYCYRRHIZA GLABRA; POGOSTEMON CABLIN TOP; SCUTELLARIA BAICALENSIS ROOT; CHINESE CINNAMON

Drug Facts

active ingredient: atractylodis rhizoma

inactive ingredient: hovenia dulcis thunberg, crataegi fructus, puerariae radix, glycyrrhizae resina, agastachis herba, scutellariae radix, cinnamon bark

PURPOSE

for the treatment of reflux esophagitis, chronic gastritis, acute gastritis, abdominal distension, indigestion, hangovers

keep out of reach of the children

INDICATIONS AND USAGE

take 3 times a day after meals with warm water

WARNINGS

keep in a dry, cool place
keep away from direct sunlight

DOSAGE AND ADMINISTRATION

do not take if you are pregnant